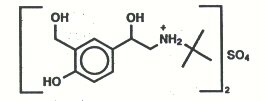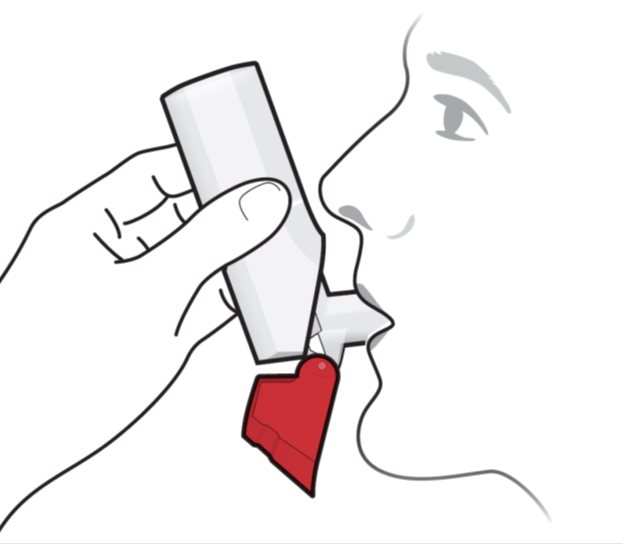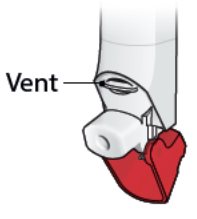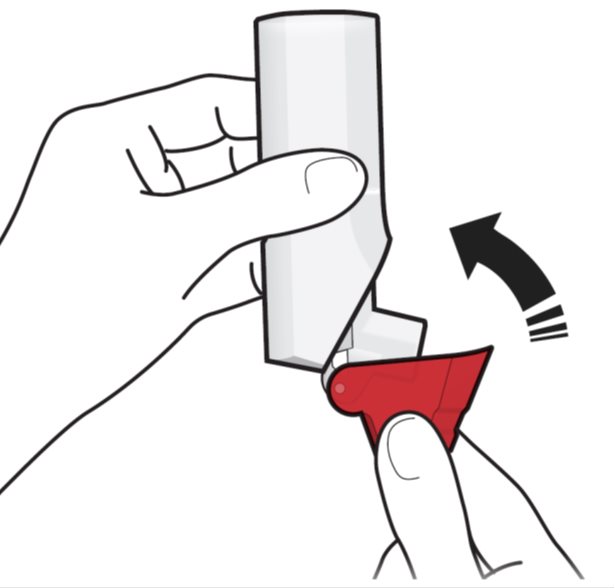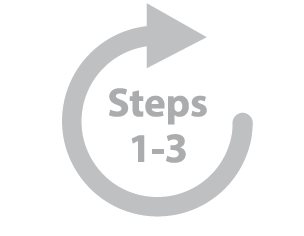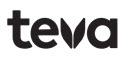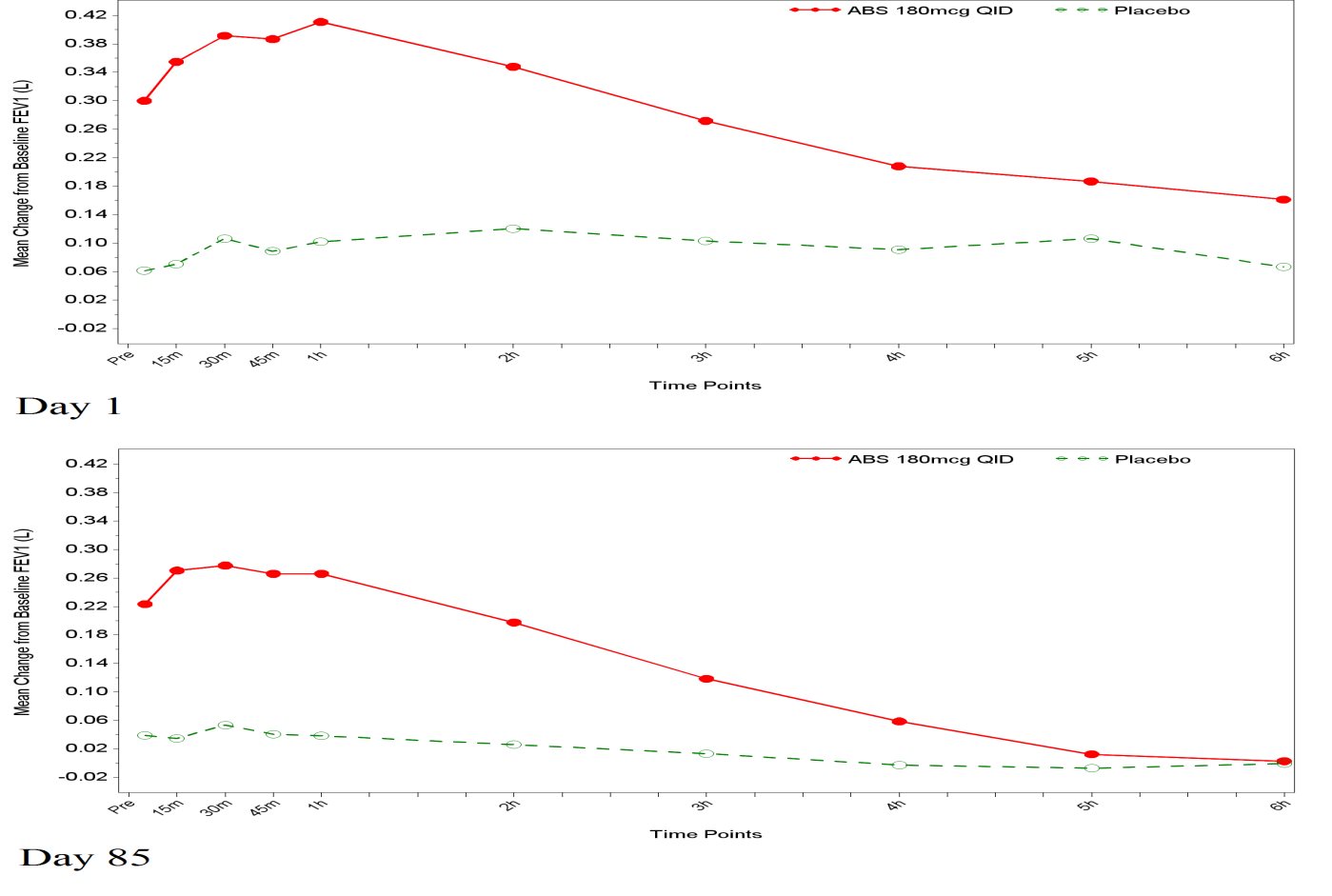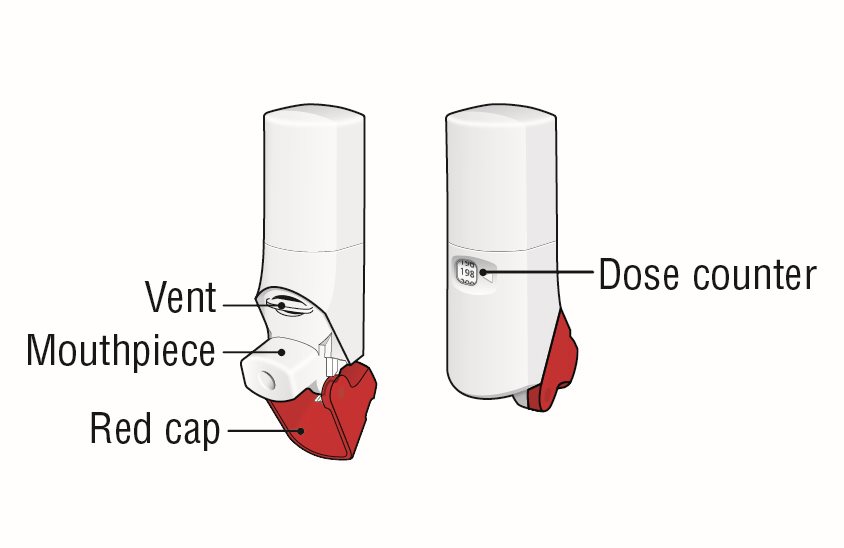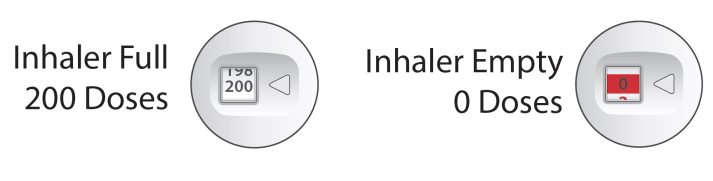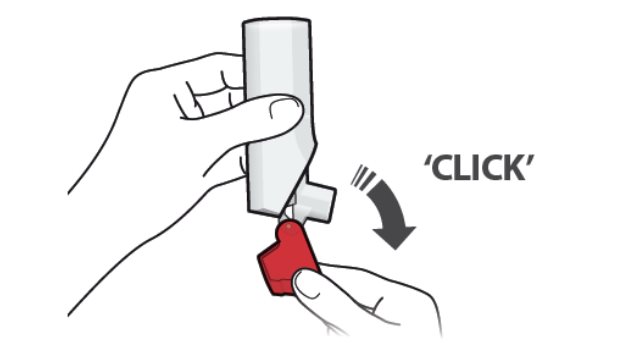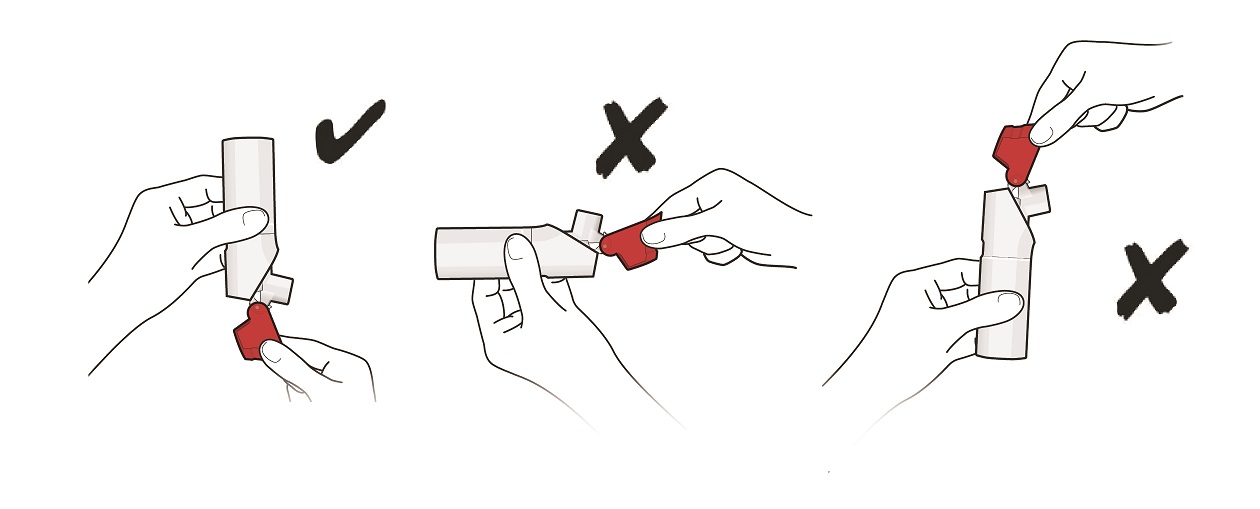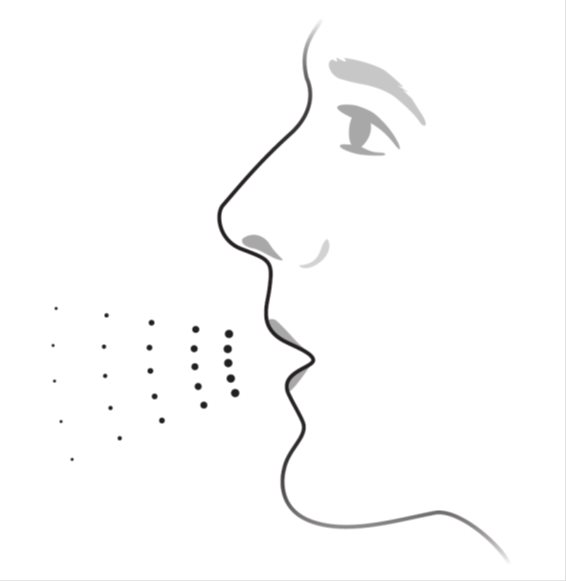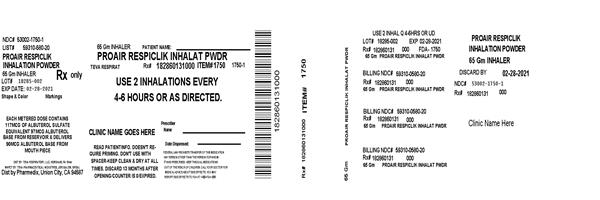 DRUG LABEL: ProAir RespiClick
NDC: 53002-1750 | Form: POWDER, METERED
Manufacturer: RPK Pharmaceuticals, Inc.
Category: prescription | Type: HUMAN PRESCRIPTION DRUG LABEL
Date: 20230607

ACTIVE INGREDIENTS: ALBUTEROL SULFATE 90 ug/1 1
INACTIVE INGREDIENTS: LACTOSE MONOHYDRATE

HIGHLIGHTS OF PRESCRIBING INFORMATION

These highlights do not include all the information needed to use PROAIR RESPICLICK safely and effectively. See full prescribing information for PROAIR RESPICLICK.
PROAIR® RESPICLICK® (albuterol sulfate) inhalation powder, for oral
inhalation use
Initial U.S. Approval: 1981

1 INDICATIONS AND USAGE

PROAIR RESPICLICK is a beta2-adrenergic agonist indicated for:

- Treatment or prevention of bronchospasm in patients 4 years of age and older with reversible obstructive airway disease. (1.1)
- Prevention of exercise-induced bronchospasm in patients 4 years of age and older. (1.2)

2 DOSAGE AND ADMINISTRATION

For oral inhalation only

- Treatment or prevention of bronchospasm in adults and children 4 years of age and older: 2 inhalations every 4 to 6 hours by oral inhalation. In some patients, 1 inhalation every 4 hours may be sufficient. (2.1)
- Prevention of exercise-induced bronchospasm in adults and children 4 years of age and older: 2 inhalations 15 to 30 minutes before exercise by oral inhalation. (2.2)
- PROAIR RESPICLICK does not require priming. (2.3)
- Do not use with a spacer or volume holding chamber. (2.3)
- Keep the inhaler clean and dry at all times. Routine maintenance is not required. If the mouthpiece needs cleaning, gently wipe the mouthpiece with a dry cloth or tissue as needed. Never wash or put any part of the inhaler in water. (2.3)
- Discard 13 months after opening the foil pouch, when the dose counter displays 0, or after the expiration date on the product, whichever comes first. (2.3)

3 DOSAGE FORMS AND STRENGTHS

Inhalation powder: dry powder inhaler that delivers 108 mcg of albuterol sulfate (equivalent to 90 mcg of albuterol base) from the mouthpiece per actuation. The inhaler is supplied for 200 inhalation doses. (3)

4 CONTRAINDICATIONS

- Patients with hypersensitivity to albuterol. (4)
- Patients with severe hypersensitivity to milk proteins. (4)

5 WARNINGS AND PRECAUTIONS

- Life-threatening paradoxical bronchospasm may occur. Discontinue PROAIR RESPICLICK immediately and treat with alternative therapy. (5.1)
- Need for more doses of PROAIR RESPICLICK than usual may be a sign of deterioration of asthma and requires reevaluation of treatment. (5.2)
- PROAIR RESPICLICK is not a substitute for corticosteroids. (5.3)
- Cardiovascular effects may occur. Use with caution in patients sensitive to sympathomimetic drugs and patients with cardiovascular or convulsive disorders. (5.4, 5.7)
- Excessive use may be fatal. Do not exceed recommended dose. (5.5)
- Immediate hypersensitivity reactions may occur. Discontinue PROAIR RESPICLICK immediately. (5.6)
- Hypokalemia and changes in blood glucose may occur. (5.7, 5.8)

6 ADVERSE REACTIONS

Most common adverse reactions (≥1% and >placebo) are back pain, pain, gastroenteritis viral, sinus headache, urinary tract infection, nasopharyngitis, oropharyngeal pain and vomiting. (6.1)

To report SUSPECTED ADVERSE REACTIONS, contact Teva Respiratory, LLC at 1-888-482-9522 or FDA at 1-800-FDA-1088 or www.fda.gov/medwatch.

7 DRUG INTERACTIONS

- Other short-acting sympathomimetic aerosol bronchodilators and adrenergic drugs: May potentiate effect. (7)
- Beta-blockers: May decrease effectiveness of PROAIR RESPICLICK and produce severe bronchospasm. Patients with asthma should not normally be treated with beta-blockers. (7.1)
- Diuretics, or non-potassium sparing diuretics: May potentiate hypokalemia or ECG changes. Consider monitoring potassium levels. (7.2)
- Digoxin: May decrease serum digoxin levels. Consider monitoring digoxin levels. (7.3)
- Monoamine oxidase (MAO) inhibitors and tricyclic antidepressants: May potentiate effect of albuterol on the cardiovascular system. Consider alternative therapy in patients taking MAOs or tricyclic antidepressants. (7.4)

FULL PRESCRIBING INFORMATION

1 INDICATIONS AND USAGE

1.1 Bronchospasm

PROAIR RESPICLICK is indicated for the treatment or prevention of bronchospasm in patients 4 years of age and older with reversible obstructive airway disease.

1.2 Exercise-Induced Bronchospasm

PROAIR RESPICLICK is indicated for the prevention of exercise-induced bronchospasm in patients 4 years of age and older.

2 DOSAGE AND ADMINISTRATION

2.1 Recommended Dosage for Bronchospasm

The recommended dosage is 2 inhalations every 4 to 6 hours by oral inhalation. More frequent administration or a larger number of inhalations is not recommended. In some patients, 1 inhalation every 4 hours may be sufficient.

2.2 Recommended Dosage for Exercise-Induced Bronchospasm

The recommended dosage is 2 inhalations 15 to 30 minutes before exercise by oral inhalation.

2.3 Administration and Maintenance Information

Administer PROAIR RESPICLICK by oral inhalation only. PROAIR RESPICLICK inhaler does not require priming. Do not use PROAIR RESPICLICK with a spacer or volume holding chamber.

Keep the inhaler clean and dry at all times. Never wash or put any part of your inhaler in water. Routine maintenance is not required. If the mouthpiece needs cleaning, gently wipe the mouthpiece with a dry cloth or tissue as needed.

2.4 Dose Counter

The PROAIR RESPICLICK inhaler has a dose counter attached to the actuator. When the patient receives the inhaler, the number 200 will be displayed. The dose counter will count down each time the inhaler is actuated. When the dose counter reaches 20, the color of the numbers will change to red to remind the patient to contact their pharmacist for a refill of medication or consult their physician for a prescription refill. When the dose counter reaches 0, the background will change to solid red. Discard PROAIR RESPICLICK 13 months after opening the foil pouch, when the dose counter displays 0 or after the expiration date on the product, whichever comes first [see Patient Counseling Information (17)].

3 DOSAGE FORMS AND STRENGTHS

Inhalation powder: a multi-dose breath-actuated dry powder inhaler that delivers 108 mcg of albuterol sulfate (equivalent to 90 mcg of albuterol base) from the mouth piece per actuation. Each inhaler is supplied for 200 inhalations.

4 CONTRAINDICATIONS

PROAIR RESPICLICK is contraindicated in patients with a history of hypersensitivity to albuterol and/or severe hypersensitivity to milk proteins. Rare cases of hypersensitivity reactions, including urticaria, angioedema, and rash have been reported after the use of albuterol sulfate. There have been reports of anaphylactic reactions in patients using inhalation therapies containing lactose [see Warnings and Precautions (5.6)].

5 WARNINGS AND PRECAUTIONS

5.1 Paradoxical Bronchospasm

PROAIR RESPICLICK can produce paradoxical bronchospasm that may be life threatening. If paradoxical bronchospasm occurs, PROAIR RESPICLICK should be discontinued immediately and alternative therapy instituted.

5.2 Deterioration of Asthma

Asthma may deteriorate acutely over a period of hours or chronically over several days or longer. If the patient needs more doses of PROAIR RESPICLICK, this may be a marker of destabilization of asthma and requires re-evaluation of the patient and treatment regimen, giving special consideration to the possible need for anti-inflammatory treatment, eg, corticosteroids.

5.3 Use of Anti-Inflammatory Agents

The use of beta-adrenergic-agonist bronchodilators alone may not be adequate to control asthma in many patients. Early consideration should be given to adding anti-inflammatory agents, e.g., corticosteroids, to the therapeutic regimen.

5.4 Cardiovascular Effects

PROAIR RESPICLICK, like other beta-adrenergic agonists, can produce clinically significant cardiovascular effects in some patients as measured by pulse rate, blood pressure, and/or symptoms. Although such effects are uncommon after administration of PROAIR RESPICLICK at recommended doses, if they occur, the drug may need to be discontinued. In addition, beta-agonists have been reported to produce ECG changes, such as flattening of the T-wave, prolongation of the QTc interval, and ST segment depression. The clinical significance of these findings is unknown. Therefore, PROAIR RESPICLICK, like all sympathomimetic amines, should be used with caution in patients with cardiovascular disorders, especially coronary insufficiency, cardiac arrhythmias, and hypertension.

5.5 Do Not Exceed Recommended Dose

Fatalities have been reported in association with excessive use of inhaled sympathomimetic drugs in patients with asthma. The exact cause of death is unknown, but cardiac arrest following an unexpected development of a severe acute asthmatic crisis and subsequent hypoxia is suspected.

5.6 Hypersensitivity Reactions including Anaphylaxis

Immediate hypersensitivity reactions may occur after administration of albuterol sulfate, as demonstrated by rare cases of urticaria, angioedema, rash, bronchospasm, anaphylaxis, and oropharyngeal edema. PROAIR RESPICLICK contains small amounts of lactose, which may contain trace levels of milk proteins. Hypersensitivity reactions including anaphylaxis, angioedema, pruritus, and rash have been reported with the use of therapies containing lactose (lactose is an inactive ingredient in PROAIR RESPICLICK). The potential for hypersensitivity must be considered in the clinical evaluation of patients who experience immediate hypersensitivity reactions while receiving PROAIR RESPICLICK.

5.7 Coexisting Conditions

PROAIR RESPICLICK, like all sympathomimetic amines, should be used with caution in patients with cardiovascular disorders, especially coronary insufficiency, cardiac arrhythmias, and hypertension; in patients with convulsive disorders, hyperthyroidism, or diabetes mellitus; and in patients who are unusually responsive to sympathomimetic amines. Clinically significant changes in systolic and diastolic blood pressure have been seen in individual patients and could be expected to occur in some patients after use of any beta-adrenergic bronchodilator. Large doses of intravenous albuterol have been reported to aggravate preexisting diabetes mellitus and ketoacidosis.

5.8 Hypokalemia

As with other beta-agonists, PROAIR RESPICLICK may produce significant hypokalemia in some patients, possibly through intracellular shunting, which has the potential to produce adverse cardiovascular effects. The decrease is usually transient, not requiring supplementation.

6 ADVERSE REACTIONS

Use of PROAIR RESPICLICK may be associated with the following:

- Paradoxical bronchospasm [see Warnings and Precautions (5.1)]
- Cardiovascular Effects [see Warnings and Precautions (5.4)]
- Immediate hypersensitivity reactions [see Warnings and Precautions (5.6)]
- Hypokalemia [see Warnings and Precautions (5.8)

6.1 Clinical Trials Experience

A total of 1289 subjects were treated with PROAIR RESPICLICK during the clinical development program. The most common adverse reactions (≥1% and > placebo) were back pain, pain, gastroenteritis viral, sinus headache, and urinary tract infection. Because clinical trials are conducted under widely varying conditions, adverse reaction rates observed in the clinical trials of a drug cannot be directly compared to rates in the clinical trials of another drug and may not reflect the rates observed in practice.

Adults and Adolescents 12 years of Age and Older: The adverse reaction information presented in Table 1 below concerning PROAIR RESPICLICK is derived from the 12-week blinded treatment period of three studies which compared PROAIR RESPICLICK 180 mcg four times daily with a double-blinded matched placebo in 653 asthmatic patients 12 to 76 years of age.

Table 1: Adverse Reactions Experienced by Greater Than or Equal to 1.0% of Adult and Adolescent Patients in the PROAIR RESPICLICK Group and Greater Than Placebo in three 12-Week Clinical Trials^1

Preferred Term | Number (%) of patients
Preferred Term | PROAIR RESPICLICK 180 mcg QID N=321 | Placebo N=333
Back pain | 6 (2%) | 4 (1%)
Pain | 5 (2%) | 2 (<1%)
Gastroenteritis viral | 4 (1%) | 3 (<1%)
Sinus headache | 4 (1%) | 3 (<1%)
Urinary tract infection | 4 (1%) | 3 (<1%)

1. This table includes all adverse events (whether considered by the investigator drug related or unrelated to drug) which occurred at an incidence rate of greater than or equal to 1.0% in the PROAIR RESPICLICK group and greater than placebo.

In a long-term study of 168 patients treated with PROAIR RESPICLICK for up to 52 weeks (including a 12-week double-blind period), the most commonly reported adverse events greater than or equal to 5% were upper respiratory infection, nasopharyngitis, sinusitis, bronchitis, cough, oropharyngeal pain, headache, and pyrexia.

In a small cumulative dose study, tremor, palpitations, and headache were the most frequently occurring (≥5%) adverse events.

Pediatric Patients 4 to 11 Years of Age: The adverse reaction information presented in Table 2 below concerning PROAIR RESPICLICK is derived from a 3‑week pediatric clinical trial which compared PROAIR RESPICLICK 180 mcg albuterol 4 times daily with a double‑blinded matched placebo in 185 asthmatic patients 4 to 11 years of age.

Table 2: Adverse Reactions Experienced by Greater Than or Equal to 2.0% of Patients 4 to 11 Years of Age in the PROAIR RESPICLICK Group and Greater Than Placebo in the 3 Week Trial

Preferred Term | Number (%) of patients
Preferred Term | PROAIR RESPICLICK 180 mcg QID N=93 | Placebo N=92
Nasopharyngitis | 2 (2%) | 1 (1%)
Oropharyngeal pain | 2 (2%) | 1 (1%)
Vomiting | 3 (3%) | 1 (1%)

6.2 Postmarketing Experience

In addition to the adverse reactions reported from clinical trials with PROAIR RESPICLICK, the following adverse events have been reported during use of other inhaled albuterol sulfate products: Urticaria, angioedema, rash, bronchospasm, hoarseness, oropharyngeal edema, and arrhythmias (including atrial fibrillation, supraventricular tachycardia, extrasystoles), rare cases of aggravated bronchospasm, lack of efficacy, asthma exacerbation (potentially fatal), muscle cramps, and various oropharyngeal side-effects such as throat irritation, altered taste, glossitis, tongue ulceration, and gagging. Because these reactions are reported voluntarily from a population of uncertain size, it is not always possible to reliably estimate their frequency or establish a causal relationship to drug exposure.

In addition, albuterol, like other sympathomimetic agents, can cause adverse reactions such as: angina, hypertension or hypotension, palpitations, central nervous system stimulation, insomnia, headache, nervousness, tremor, muscle cramps, drying or irritation of the oropharynx, hypokalemia, hyperglycemia, and metabolic acidosis.

7 DRUG INTERACTIONS

Other short-acting sympathomimetic bronchodilators should not be used concomitantly with PROAIR RESPICLICK. If additional adrenergic drugs are to be administered by any route, they should be used with caution to avoid deleterious cardiovascular effects.

7.1 Beta-Blockers

Beta-adrenergic-receptor blocking agents not only block the pulmonary effect of beta-agonists, such as PROAIR RESPICLICK, but may produce severe bronchospasm in asthmatic patients. Therefore, patients with asthma should not normally be treated with beta-blockers. However, under certain circumstances, eg, as prophylaxis after myocardial infarction, there may be no acceptable alternatives to the use of beta-adrenergic-blocking agents in patients with asthma. In this setting, consider cardioselective beta-blockers, although they should be administered with caution.

7.2 Diuretics

The ECG changes and/or hypokalemia which may result from the administration of non-potassium sparing diuretics (such as loop or thiazide diuretics) can be acutely worsened by beta-agonists, especially when the recommended dose of the beta-agonist is exceeded. Although the clinical significance of these effects is not known, caution is advised in the coadministration of beta-agonists with non-potassium sparing diuretics. Consider monitoring potassium levels.

7.3 Digoxin

Mean decreases of 16% and 22% in serum digoxin levels were demonstrated after single dose intravenous and oral administration of albuterol, respectively, to normal volunteers who had received digoxin for 10 days. The clinical significance of these findings for patients with obstructive airway disease who are receiving albuterol and digoxin on a chronic basis is unclear. Nevertheless, it would be prudent to carefully evaluate the serum digoxin levels in patients who are currently receiving digoxin and PROAIR RESPICLICK.

7.4 Monoamine Oxidase Inhibitors or Tricyclic Antidepressants

PROAIR RESPICLICK should be administered with extreme caution to patients being treated with monoamine oxidase inhibitors or tricyclic antidepressants, or within 2 weeks of discontinuation of such agents, because the action of albuterol on the cardiovascular system may be potentiated. Consider alternative therapy in patients taking MAO inhibitors or tricyclic antidepressants.

8 USE IN SPECIFIC POPULATIONS

8.1 Pregnancy

Risk Summary

There are no randomized clinical studies of use of albuterol during pregnancy. Available data from published epidemiological studies and postmarketing case reports of pregnancy outcomes following inhaled albuterol use do not consistently demonstrate a risk of major birth defects or miscarriage. There are clinical considerations with use of albuterol in pregnant women [see Clinical Considerations]. In animal reproduction studies, when albuterol sulfate was administered subcutaneously to pregnant mice there was evidence of cleft palate at less than and up to 9 times the maximum recommended human daily inhalation dose (MRHDID) [see Data].

The estimated background risk of major birth defects and miscarriage for the indicated population(s) are unknown. In the U.S. general population, the estimated risk of major birth defects and miscarriage in clinically recognized pregnancies is 2 to 4% and 15 to 20%, respectively.

Clinical Considerations

Disease-Associated Maternal and/or Embryo/Fetal Risk

In women with poorly or moderately controlled asthma, there is an increased risk of preeclampsia in the mother and prematurity, low birth weight, and small for gestational age in the neonate. Pregnant women should be closely monitored and medication adjusted as necessary to maintain optimal control.

Labor or Delivery

Because of the potential for beta-agonist interference with uterine contractility, use of PROAIR RESPICLICK for relief of bronchospasm during labor should be restricted to those patients in whom the benefits clearly outweigh the risk. PROAIR RESPICLICK has not been approved for the management of pre-term labor. Serious adverse reactions, including pulmonary edema, have been reported during or following treatment of premature labor with beta2-agonists, including albuterol.

Data

Animal Data

In a mouse reproduction study, subcutaneously administered albuterol sulfate produced cleft palate formation in 5 of 111 (4.5%) fetuses at an exposure nine-tenths the maximum recommended human dose (MRHDID) for adults (on a mg/m^2 basis at a maternal dose of 0.25 mg/kg) and in 10 of 108 (9.3%) fetuses at approximately 9 times the MRHDID (on a mg/m^2 basis at a maternal dose of 2.5 mg/kg). Similar effects were not observed at approximately one-eleventh the MRHDID for adults (on a mg/m^2 basis at a maternal dose of 0.025 mg/kg). Cleft palate also occurred in 22 of 72 (30.5%) fetuses from females treated subcutaneously with isoproterenol (positive control).

In a rabbit reproduction study, orally administered albuterol sulfate induced cranioschisis in 7 of 19 fetuses (37%) at approximately 750 times the MRHDID (on a mg/m^2 basis at a maternal dose of 50 mg/kg).

In a rat reproduction study, an albuterol sulfate/HFA-134a formulation administered by inhalation did not produce any teratogenic effects at exposures approximately 80 times the MRHDID (on a mg/m^2 basis at a maternal dose of 10.5 mg/kg).

A study in which pregnant rats were dosed with radiolabeled albuterol sulfate demonstrated that drug-related material is transferred from the maternal circulation to the fetus.

8.2 Lactation

Risk Summary

There are no available data on the presence of albuterol in human milk, the effects on the breastfed child, or the effects on milk production. However, plasma levels of albuterol after inhaled therapeutic doses are low in humans, and if present in breast milk, albuterol has a low oral bioavailability [see Clinical Pharmacology (12.3)].

The developmental and health benefits of breastfeeding should be considered along with the mother’s clinical need for albuterol and any potential adverse effects on the breastfed child from albuterol or from the underlying maternal condition.

8.4 Pediatric Use

The safety and effectiveness of PROAIR RESPICLICK for the treatment or prevention of bronchospasm with reversible obstructive airway disease have been established in pediatric patients 12 to 17 years of age. Use of PROAIR RESPICLICK for this indication is supported by evidence from two 12-week clinical trials in 318 patients 12 years of age and older with asthma comparing doses of 180 mcg four times daily with placebo, one long-term safety study in children 12 years of age and older, and one single-dose crossover study comparing doses of 90 and 180 mcg with albuterol sulfate inhalation aerosol (ProAir® HFA) in 71 patients [see Clinical Studies (14.1)].

The safety and effectiveness of PROAIR RESPICLICK for treatment of exercise-induced bronchospasm have been established in children 12 years of age and older. Use of PROAIR RESPICLICK for this indication is supported by evidence from one single-dose crossover study in 38 patients age 16 and older with exercise-induced bronchospasm comparing doses of 180 mcg with placebo [see Clinical Studies (14.2)]. The safety profile for patients ages 12 to 17 was consistent with the overall safety profile seen in these studies.

The safety of PROAIR RESPICLICK in children 4 to 11 years of age is based on two single-dose, controlled, crossover studies: one with 61 patients comparing doses of 90 and 180 mcg with matched placebo and albuterol HFA MDI and one with 15 patients comparing a dose of 180 mcg with matched albuterol HFA MDI; and one 3-week clinical trial in 185 patients 4 to 11 years of age with asthma comparing a dose of 180 mcg four times daily with matched albuterol HFA MDI. The effectiveness of PROAIR RESPICLICK in children 4 to 11 years with exercise-induced bronchospasm is extrapolated from clinical trials in patients 12 years of age and older with asthma and exercise-induced bronchospasm, based on data from a single-dose study comparing the bronchodilatory effect of PROAIR RESPICLICK 90 mcg and 180 mcg with placebo in 61 patients with asthma, and data from a 3-week clinical trial in 185 asthmatic children 4 to 11 years of age comparing a dose of 180 mcg albuterol 4 times daily with placebo [see Clinical Studies (14.1)].

The safety and effectiveness of PROAIR RESPICLICK in pediatric patients below the age of 4 years have not been established.

8.5 Geriatric Use

Clinical studies of PROAIR RESPICLICK did not include sufficient numbers of patients aged 65 and over to determine whether they respond differently from younger patients. Other reported clinical experience has not identified differences in responses between elderly and younger patients. In general, dose selection for an elderly patient should be cautious, usually starting at the low end of the dosing range, reflecting the greater frequency of decreased hepatic, renal, or cardiac function, and of concomitant disease or other drug therapy [see Warnings and Precautions (5.4, 5.7)].

All beta2-adrenergic agonists, including albuterol, are known to be substantially excreted by the kidney, and the risk of toxic reactions may be greater in patients with impaired renal function. Because elderly patients are more likely to have decreased renal function, care should be taken in dose selection, and it may be useful to monitor renal function.

10 OVERDOSAGE

The expected symptoms with overdosage are those of excessive beta-adrenergic stimulation and/or occurrence or exaggeration of any of the symptoms listed under ADVERSE REACTIONS, eg, seizures, angina, hypertension or hypotension, tachycardia with rates up to 200 beats per minute, arrhythmias, nervousness, headache, tremor, dry mouth, palpitation, nausea, dizziness, fatigue, malaise, and insomnia.

Hypokalemia may also occur. As with all sympathomimetic medications, cardiac arrest and even death may be associated with abuse of PROAIR RESPICLICK.

Treatment consists of discontinuation of PROAIR RESPICLICK together with appropriate symptomatic therapy. The judicious use of a cardioselective beta-receptor blocker may be considered, bearing in mind that such medication can produce bronchospasm. There is insufficient evidence to determine if dialysis is beneficial for overdosage of PROAIR RESPICLICK.

11 DESCRIPTION

The active ingredient of PROAIR RESPICLICK inhalation powder is albuterol sulfate, a racemic salt of albuterol. Albuterol sulfate is a beta2-adrenergic agonist. It has the chemical name α^1-[(tert-butylamino) methyl]-4-hydroxy-m-xylene-α,α'-diol sulfate (2:1) (salt), and the following chemical structure:

The molecular weight of albuterol sulfate is 576.7, and the empirical formula is (C13H21NO3)2•H2SO4. Albuterol sulfate is a white to off-white crystalline powder. It is soluble in water and slightly soluble in ethanol. Albuterol sulfate is the official U.S. Adopted Name in the United States, and salbutamol sulfate is the recommended World Health Organization international nonproprietary name.

PROAIR RESPICLICK is an inhalation-driven, multi-dose inhalation powder (dry powder inhaler) for oral inhalation only. It contains a formulation blend of albuterol sulfate with alpha-lactose monohydrate. Each actuation provides a metered dose of 2.6 mg of the formulation containing 117 mcg of albuterol sulfate (equivalent to 97 mcg of albuterol base) and lactose from the device reservoir. Under standardized in vitro test conditions with fixed flow rates ranging from 58 to 71 L/min, and with a total air volume of 2 L, the PROAIR RESPICLICK inhaler delivers 108 mcg of albuterol sulfate (equivalent to 90 mcg of albuterol base) with lactose from the mouthpiece. The actual amount of drug delivered to the lung will depend on patient factors, such as inspiratory flow profile. In a study that investigated the peak inspiratory flow rate (PIFR) in asthma (n=27, ages 12 to 17 years old and n=50, ages 18 to 45 years old) and COPD (n=50, over 50 years old) patients, the mean PIFR achieved by subjects was >60 L/min (range = 31 to 110 L/min.), indicating that patients would be able to achieve the required inspiratory flow to operate the MDPI device correctly. The inhaler is provided for 200 actuations (inhalations).

12 CLINICAL PHARMACOLOGY

12.1 Mechanism of Action

Albuterol sulfate is a beta2-adrenergic agonist. The pharmacologic effects of albuterol sulfate are attributable to activation of beta2-adrenergic receptors on airway smooth muscle. Activation of beta2-adrenergic receptors leads to the activation of adenylcyclase and to an increase in the intracellular concentration of cyclic-3',5’‑adenosine monophosphate (cyclic AMP). This increase of cyclic AMP is associated with the activation of protein kinase A, which in turn inhibits the phosphorylation of myosin and lowers intracellular ionic calcium concentrations, resulting in muscle relaxation. Albuterol relaxes the smooth muscle of all airways, from the trachea to the terminal bronchioles. Albuterol acts as a functional antagonist to relax the airway irrespective of the spasmogen involved, thus protecting against all bronchoconstrictor challenges. Increased cyclic AMP concentrations are also associated with the inhibition of release of mediators from mast cells in the airway. While it is recognized that beta2-adrenergic receptors are the predominant receptors on bronchial smooth muscle, data indicate that there are beta-receptors in the human heart, 10% to 50% of which are cardiac beta2-adrenergic receptors. The precise function of these receptors has not been established [see Warnings and Precautions (5.4)].

Albuterol has been shown in most controlled clinical trials to have more effect on the respiratory tract, in the form of bronchial smooth muscle relaxation, than isoproterenol at comparable doses while producing fewer cardiovascular effects. However, inhaled albuterol, like other beta-adrenergic agonist drugs, can produce a significant cardiovascular effect in some patients, as measured by pulse rate, blood pressure, symptoms, and/or electrocardiographic changes [see Warnings and Precautions (5.4)].

12.2 Pharmacodynamics

In a pharmacodynamic (PD) trial conducted in 47 patients, the PD and safety profiles were similar for PROAIR RESPICLICK and ProAir HFA. Comparable changes from baseline in the PD measures (serum glucose and potassium concentrations, QTcB, QTcF, heart rate, systolic blood pressure, and diastolic blood pressure) were observed following cumulative dose administration up to 1440 mcg of both PROAIR RESPICLICK and ProAir HFA. The overall safety, efficacy and PD profile of PROAIR RESPICLICK and ProAir HFA were comparable.

Following 90 or 180 mcg single-dose inhalation, the bronchodilatory effect of PROAIR RESPICLICK was significantly greater than placebo and comparable to that of ProAir HFA in patients 12 years of age and older (N=71) and pediatric patients 4 to 11 years of age (N=61) with persistent asthma.

Cardiac Electrophysiology

As with other beta2-adrenergic agonists, PROAIR RESPICLICK prolonged QT intervals following a 1440 mcg cumulative dose. The prolongation was comparable to that of ProAir HFA.

12.3 Pharmacokinetics

Absorption

Albuterol was rapidly absorbed into the systemic circulation with peak plasma concentrations occurring at half an hour following single- or multiple-dose oral inhalation(s) of PROAIR RESPICLICK. In a cumulative dose study, the AUC0-t was comparable between PROAIR RESPICLICK group and ProAir HFA group; Cmax value was approximately one-third higher in PROAIR RESPICLICK group than ProAir HFA group.

Distribution

The volume of distribution has not been determined for PROAIR RESPICLICK. Published literature suggests that albuterol exhibits low in vitro plasma protein binding (10%).

Elimination

The accumulation ratio (~1.6 fold) was observed following one week QID dosing. The corresponding effective half-life was approximately 5 hours, which was consistent with the elimination half-life following both single- or multiple-dose administration.

Metabolism

Information available in the published literature suggests that the primary enzyme responsible for the metabolism of albuterol in humans is SULTIA3 (sulfotransferase). When racemic albuterol was administered either intravenously or via inhalation after oral charcoal administration, there was a 3- to 4-fold difference in the area under the concentration-time curves between the (R)- and (S)-albuterol enantiomers, with (S)-albuterol concentrations being consistently higher. However, without charcoal pretreatment, after either oral or inhalation administration the differences were 8- to 24-fold, suggesting that the (R)-albuterol is preferentially metabolized in the gastrointestinal tract, presumably by SULTIA3.

Excretion

The primary route of elimination of albuterol is through renal excretion (80% to 100%) of either the parent compound or the primary metabolite. Less than 20% of the drug is detected in the feces. Following intravenous administration of racemic albuterol, between 25% and 46% of the (R)-albuterol fraction of the dose was excreted as unchanged (R)-albuterol in the urine.

Specific Populations

No pharmacokinetic studies for PROAIR RESPICLICK have been conducted in neonates or elderly subjects. The systemic exposure in children 6 to 11 years of age is similar to that of adults following 180 mcg single dose inhalation of PROAIR RESPICLICK. The influence of gender or race on the pharmacokinetics of PROAIR RESPICLICK has not been studied.

Patients with Renal Impairment: The effect of renal impairment on the pharmacokinetics of albuterol was evaluated in 5 subjects with creatinine clearance of 7 to 53 mL/min, and the results were compared with those from healthy volunteers. Renal disease had no effect on the half-life, but there was a 67% decline in albuterol clearance. Caution should be used when administering high doses of PROAIR RESPICLICK to patients with renal impairment [see Use in Specific Populations (8.5)].

Patients with Hepatic Impairment: The effect of hepatic impairment on the pharmacokinetics of PROAIR RESPICLICK has not been evaluated.

Drug Interaction Studies: In vitro and in vivo drug interaction studies have not been conducted with PROAIR RESPICLICK. Known clinically significant drug interactions are outlined in Drug Interactions (7).

13 NONCLINICAL TOXICOLOGY

13.1 Carcinogenesis, Mutagenesis, Impairment of Fertility

In a 2-year study in Sprague-Dawley rats, albuterol sulfate caused a dose-related increase in the incidence of benign leiomyomas of the mesovarium at and above dietary doses of 2 mg/kg (approximately 15 times and 6 times the maximum recommended daily inhalation dose (MRHDID) for adults and children, respectively, on a mg/m^2 basis). In another study this effect was blocked by the coadministration of propranolol, a non-selective beta-adrenergic antagonist. In an 18-month study in CD-1 mice, albuterol sulfate showed no evidence of tumorigenicity at dietary doses of up to 500 mg/kg (approximately 1,900 times and 740 times the MRHDID for adults and children, respectively, on a mg/m^2 basis). In a 22-month study in Golden Hamsters, albuterol sulfate showed no evidence of tumorigenicity at dietary doses of up to 50 mg/kg (approximately 250 times and 100 times the MRHDID for adults and children, respectively, on a mg/m^2 basis).

Albuterol sulfate was not mutagenic in the Ames test or a mutation test in yeast. Albuterol sulfate was not clastogenic in a human peripheral lymphocyte assay or in an AH1 strain mouse micronucleus assay.

Reproduction studies in rats demonstrated no evidence of impaired fertility at oral doses up to 50 mg/kg (approximately 380 times the MRHDID for adults on a mg/m^2 basis).

13.2 Animal Toxicology and/or Pharmacology

Preclinical: Intravenous studies in rats with albuterol sulfate have demonstrated that albuterol crosses the blood-brain barrier and reaches brain concentrations amounting to approximately 5% of the plasma concentrations. In structures outside the blood-brain barrier (pineal and pituitary glands), albuterol concentrations were found to be 100 times those in the whole brain.

Studies in laboratory animals (minipigs, rodents, and dogs) have demonstrated the occurrence of cardiac arrhythmias and sudden death (with histologic evidence of myocardial necrosis) when β‑agonists and methylxanthines were administered concurrently. The clinical significance of these findings is unknown.

14 CLINICAL STUDIES

14.1 Bronchospasm Associated with Asthma

Adult and Adolescent Patients 12 Years of Age and Older

In two 12-week, randomized, double-blind, placebo-controlled studies of identical design (Study 1 and Study 2), PROAIR RESPICLICK (153 patients) was compared to a matched placebo dry powder inhaler (163 patients) in asthmatic patients 12 to 76 years of age at a dose of 180 mcg albuterol four times daily. Patients were maintained on inhaled corticosteroid treatment. Serial FEV1 measurements, shown below in Figure 1 as average of the mean changes from test-day baseline at Day 1 and Day 85, demonstrated that two inhalations of PROAIR RESPICLICK produced significantly greater improvement in FEV1 AUC0‑6hr over the pre-treatment value than placebo in Study 1. Consistent results were observed in Study 2.

Figure 1: FEV1 as Mean Change from Test-Day, Pre-Dose Baseline in a 12-Week Clinical Trial (Study 1)

In Study 1, 44 of 78 patients treated with PROAIR RESPICLICK achieved a 15% increase in FEV1 within 30 minutes post‑dose on Day 1. The median time to onset was 5.7 minutes, and median duration of effect as measured by a 15% increase was approximately 2 hours. Consistent results were observed in Study 2. In a double‑blind, randomized, placebo–controlled, single‑dose crossover study evaluating PROAIR RESPICLICK and ProAir HFA in 71 adult and adolescent subjects ages 12 and older with persistent asthma, PROAIR RESPICLICK had bronchodilator efficacy that was significantly greater than placebo at administered doses of 90 and 180 mcg.

Pediatric Patients 4 to 11 Years of Age

In a 3‑week, randomized, double‑blind, placebo-controlled trial, PROAIR RESPICLICK (92 patients) was compared to a matched placebo (92 patients) in asthmatic children 4 to 11 years of age at a dose of 180 mcg albuterol four times daily. Serial FEV1 measurements, expressed as the baseline-adjusted percent-predicted FEV1 AUC0‑6h over the 3‑week treatment period, demonstrated that 2 inhalations of PROAIR RESPICLICK produced significantly greater improvement in FEV1 over the pre-treatment value than the matched placebo.

In this study, 48 of 92 patients treated with PROAIR RESPICLICK achieved a 15% increase in FEV1 within 30 minutes post-dose on Day 1. The median time to onset was 5.9 minutes, and the median duration of effect as measured by a 15% increase was approximately 1 hour.

In a placebo-controlled, single-dose, crossover study in 61 patients 4 to 11 years of age, PROAIR RESPICLICK, administered at albuterol doses of 90 and 180 mcg, was compared with a matched placebo and with albuterol HFA MDI. PROAIR RESPICLICK provided similar bronchodilation when administered as one or two inhalations (baseline-adjusted percent-predicted serial FEV1 observed over 6 hours post-dose), whereas two inhalations from albuterol HFA MDI provided significantly greater bronchodilation compared to a single inhalation.

14.2 Exercise-Induced Bronchospasm

In a randomized, single-dose, crossover study in 38 adult and adolescent patients with exercise-induced bronchospasm (EIB), two inhalations of PROAIR RESPICLICK taken 30 minutes before exercise prevented EIB for the hour following exercise (defined as the maintenance of FEV1 within 80% of post-dose, pre-exercise baseline values) in 97% (37 of 38) of patients as compared to 42% (16 of 38) of patients when they received placebo.

Patients who participated in these clinical trials were allowed to use concomitant steroid therapy.

16 HOW SUPPLIED/STORAGE AND HANDLING

Product: 53002-1750

NDC: 53002-1750-1 200 POWDER, METERED in a INHALER / 1 in a BOX

17 PATIENT COUNSELING INFORMATION

Advise the patient to read the FDA-approved patient labeling (Patient Information and Instructions for Use). Patients should be given the following information:

Frequency of Use

The action of PROAIR RESPICLICK should last for 4 to 6 hours. Instruct patients to not use PROAIR RESPICLICK more frequently than recommended. Instruct patients to not increase the dose or frequency of doses of PROAIR RESPICLICK without consulting the physician. If patients find that treatment with PROAIR RESPICLICK becomes less effective for symptomatic relief, symptoms become worse, and/or they need to use the product more frequently than usual, they should seek medical attention immediately [see Warnings and Precautions (5.2)].

Caring for and Storing the Inhaler

Instruct patients to not open their inhaler unless they are taking a dose. Repeated opening and closing the cover without taking medication will waste medication and may damage the inhaler.

Advise patients to keep their inhaler dry and clean at all times. Never wash or put any part of the inhaler in water. Patient should replace inhaler if washed or placed in water.

Routine maintenance is not required. If the mouthpiece needs cleaning, instruct patients to gently wipe the mouthpiece with a dry cloth or tissue as needed.

Instruct patients to store the inhaler at room temperature and to avoid exposure to extreme heat, cold, or humidity.

Instruct patients to never take the inhaler apart.

Inform patients that PROAIR RESPICLICK has a dose counter. When the patient receives the inhaler, the number 200 will be displayed. The dose counter will count down each time the mouthpiece cap is opened and closed. The dose counter window displays the number of actuations left in the inhaler in units of two (eg, 200, 198, 196, etc). When the counter displays 20, the color of the numbers will change to red to remind the patient to contact their pharmacist for a refill of medication or consult their physician for a prescription refill. When the dose counter reaches 0, the background will change to solid red. Inform patients to discard PROAIR RESPICLICK when the dose counter displays 0 or after the expiration date on the product, whichever comes first [see Dosage and Administration (2.3), (2.4)].

Paradoxical Bronchospasm

Inform patients that PROAIR RESPICLICK can produce paradoxical bronchospasm. Instruct patients to discontinue PROAIR RESPICLICK if paradoxical bronchospasm occurs [see Warnings and Precautions (5.1)].

Concomitant Drug Use

Inform patients that, while they are taking PROAIR RESPICLICK, they should take other inhaled drugs and asthma medications only as directed by a physician [see Drug Interactions (7)].

Common Adverse Events

Common adverse effects of treatment with inhaled albuterol include palpitations, chest pain, rapid heart rate, tremor, and nervousness.

Pregnancy

Inform patients who are pregnant or nursing that they should contact their physician about the use of PROAIR RESPICLICK [see Use in Specific Populations (8.1)].

General Information on Use

Effective and safe use of PROAIR RESPICLICK includes an understanding of the way that it should be administered. Do not use a spacer or volume holding chamber with PROAIR RESPICLICK. Patients should be instructed on the proper use of the inhaler. See the FDA-approved Patient Information and Patient Instructions for Use. Discard PROAIR RESPICLICK 13 months after opening the foil pouch, when the dose counter displays 0 or after the expiration date on the product, whichever comes first.

In general, the technique for administering PROAIR RESPICLICK to children is similar to that for adults. Children should use PROAIR RESPICLICK under adult supervision, as instructed by the patient’s physician.

Distributed by:

Teva Pharmaceuticals USA, Inc.

Parsippany, NJ 07054

©2020, Teva Respiratory, LLC. All rights reserved.

United States Patent Nos. 6701917, 6718972, 6748947, 6871646, 7540282, 8006690, 8651103, 8978966, 9216260, 9463288, 9731087

PROR-006

Rev. 09/2020

PATIENT INFORMATION

PROAIR® RESPICLICK® (prō´ār res-pē-klik)

(albuterol sulfate)

inhalation powder

What is PROAIR RESPICLICK?

PROAIR RESPICLICK is a prescription medicine used in people 4 years of age and older to:

- treat or prevent bronchospasm in people who have reversible obstructive airway disease
- prevent exercise-induced bronchospasm

It is not known if PROAIR RESPICLICK is safe and effective in children under 4 years of age.

Do not use PROAIR RESPICLICK if you are allergic to albuterol sulfate, lactose, milk proteins, or any of the ingredients in PROAIR RESPICLICK. See the end of this leaflet for a complete list of ingredients in PROAIR RESPICLICK.

Before using PROAIR RESPICLICK, tell your doctor about all of your medical conditions, including if you:

- have heart problems
- have high blood pressure (hypertension)
- have convulsions (seizures)
- have thyroid problems
- have diabetes
- have low potassium levels in your blood
- are pregnant or plan to become pregnant. It is not known if PROAIR RESPICLICK will harm your unborn baby. Talk to your doctor if you are pregnant or plan to become pregnant.
- are breastfeeding or plan to breastfeed. It is not known if PROAIR RESPICLICK passes into your breast milk. Talk to your doctor about the best way to feed your baby if you are using PROAIR RESPICLICK.

Tell your doctor about all the medicines you take, including prescription and over-the-counter medicines, vitamins, and herbal supplements.

PROAIR RESPICLICK and other medicines may affect each other and cause side effects. PROAIR RESPICLICK may affect the way other medicines work, and other medicines may affect the way PROAIR RESPICLICK works.

Especially tell your doctor if you take:

● other inhaled medicines or asthma medicines ● digoxin

● beta blocker medicines ● monoamine oxidase inhibitors

● diuretics ● tricyclic antidepressants

Ask your doctor or pharmacist for a list of these medicines if you are not sure.

Know the medicines you take. Keep a list of them to show your doctor and pharmacist when you get a new medicine.

How should I use PROAIR RESPICLICK?

- For detailed instructions on how to use the inhaler, see “Instructions for Use” at the end of this Patient Information.
- Use PROAIR RESPICLICK exactly as your doctor tells you to use it.
- If your child needs to use PROAIR RESPICLICK, watch your child closely to make sure your child uses the inhaler correctly. Your doctor will show you how your child should use PROAIR RESPICLICK.
- Each dose of PROAIR RESPICLICK should last up to 4 hours to 6 hours.
- Do not increase your dose or take extra doses of PROAIR RESPICLICK without first talking to your doctor.
- Do not use a spacer or volume holding chamber with PROAIR RESPICLICK.
- PROAIR RESPICLICK does not need priming.
- Get medical help right away if PROAIR RESPICLICK no longer helps your symptoms.
- Get medical help right away if your symptoms get worse or if you need to use your inhaler more often.
- While you are using PROAIR RESPICLICK, do not use other inhaled rescue medicines and asthma medicines unless your doctor tells you to do so.
- Call your doctor if your asthma symptoms like wheezing and trouble breathing become worse over a few hours or days. Your doctor may need to give you another medicine (for example, corticosteroids) to treat your symptoms.

What are the possible side effects of PROAIR RESPICLICK?

PROAIR RESPICLICK may cause serious side effects, including:

- worsening trouble breathing, coughing and wheezing (paradoxical bronchospasm). If this happens stop using PROAIR RESPICLICK and call your doctor or get emergency help right away.
- heart problems, including faster heart rate and higher blood pressure
- possible death in people with asthma who use too much PROAIR RESPICLICK
- allergic reactions. Call your doctor right away if you have the following symptoms of an allergic reaction:

○ itchy skin ○ rash

○ swelling beneath your skin or in your throat ○ worsening trouble breathing

- worsening of other medical problems in people who also use PROAIR RESPICLICK including increases in blood sugar
- low potassium levels in your blood

The most common side effects of PROAIR RESPICLICK include:

● back pain ● fast heart rate

● pain ● shakiness

● upset stomach ● nervousness

● sinus headache ● headache

● urinary tract infection ● dizziness

● your heart feels like it is pounding or racing (palpitations) ● sore throat

● chest pain ● runny nose

● vomiting

These are not all of the possible side effects of PROAIR RESPICLICK.

Call your doctor for medical advice about side effects. You may report side effects to FDA at 1-800-FDA-1088.

How should I store PROAIR RESPICLICK?

- Store PROAIR RESPICLICK at room temperature between 59ºF and 77ºF (15ºC and 25ºC).
- Avoid exposure to extreme heat, cold, or humidity.
- Keep the cap on the inhaler closed during storage.
- Keep your PROAIR RESPICLICK inhaler dry and clean at all times.
- Do not wash or put any part of your PROAIR RESPICLICK inhaler in water. Replace your inhaler if washed or placed in water.

Keep PROAIR RESPICLICK and all medicines out of the reach of children.

General information about the safe and effective use of PROAIR RESPICLICK.

Medicines are sometimes prescribed for purposes other than those listed in a Patient Information leaflet. Do not use PROAIR RESPICLICK for a condition for which it was not prescribed. Do not give PROAIR RESPICLICK to other people, even if they have the same symptoms that you have. It may harm them.

You can ask your pharmacist or doctor for information about PROAIR RESPICLICK that was written for health professionals.

For more information, go to www.MyProAir.com or call 1-888-482-9522.

What are the ingredients in PROAIR RESPICLICK?

Active ingredient: albuterol sulfate

Inactive ingredients: lactose (may contain milk proteins)

Distributed by:

Teva Pharmaceuticals USA, Inc.

Parsippany, NJ 07054

©2020 Teva Respiratory, LLC. All rights reserved.

PRORPL-005

This Patient Information has been approved by the U.S. Food and Drug Administration.

Revised: 09/2020

Instructions for Use

PROAIR® RESPICLICK® (prō´ār res-pē-klik)

(albuterol sulfate)

inhalation powder

Your PROAIR RESPICLICK Inhaler

When you are ready to use PROAIR RESPICLICK for the first time, remove the PROAIR RESPICLICK inhaler from the foil pouch.

There are 2 main parts of your PROAIR RESPICLICK inhaler including:

- the white inhaler with the mouthpiece. See Figure A.
- the red cap that covers the mouthpiece of the inhaler. See Figure A.

There is a dose counter in the back of the inhaler with a viewing window that shows you how many doses of medicine you have left. See Figure A.

Figure A

- Your PROAIR RESPICLICK inhaler contains 200 doses (inhalations). See Figure B.
- The dose counter shows the number of doses left in your inhaler.
- When there are 20 doses left, the dose counter will change to red, and you should refill your prescription or ask your doctor for another prescription.
- When the dose counter displays ‘0,’ your inhaler is empty, and you should stop using the inhaler and throw it away. See Figure B.

Figure B

IMPORTANT:

- Always close the cap after each inhalation so your inhaler will be ready for you to take your next dose. Do not open the cap unless you are ready for your next dose.
- You will hear a “click” sound when the cap is opened fully. If you do not hear the “click” sound the inhaler may not be activated to give you a dose of medicine.
- PROAIR RESPICLICK does not have an activation button or medicine canister. When you open the cap, a dose of PROAIR will be activated for delivery of the medicine.
- In general, the technique for administering PROAIR RESPICLICK to children is similar to that for adults. Children should use PROAIR RESPICLICK under adult supervision, as instructed by the patient’s physician.
- Do not use a spacer or volume holding chamber with PROAIR RESPICLICK. PROAIR RESPICLICK does not need priming.

Using your PROAIR RESPICLICK inhaler:

Important: Make sure the red cap is closed before you start using your inhaler.

Step 1. Open

- Hold the inhaler upright and open the red cap fully until you feel and hear a “click”. See Figure C.
- Each time you open the red cap and it “clicks”, a dose of PROAIR RESPICLICK is ready to be inhaled.

Figure C

Remember:

- For the correct use of PROAIR RESPICLICK, hold the inhaler upright as you open the red cap. See Figure D.
- Do not hold the inhaler in any other way as you open the red cap.
- Do not open the red cap until you are ready to take a dose of PROAIR RESPICLICK.

Figure D

Step 2. Inhale

- Before you inhale, breathe out (exhale) through your mouth and push as much air from your lungs as you can. See Figure E.
- Do not exhale into the inhaler mouthpiece.

Figure E

- Put the mouthpiece in your mouth and close your lips tightly around it. See Figure F.

Figure F

- Do not block the vent above the mouthpiece with your lips or fingers. See Figure G.

Figure G

- Breathe in quickly and deeply through your mouth, to deliver the dose of medicine to your lungs.
- Remove the inhaler from your mouth.
- Hold your breath for about 10 seconds or for as long as you comfortably can.
- Your PROAIR RESPICLICK inhaler delivers your dose of medicine as a very fine powder that you may or may not taste or feel. Do not take an extra dose from the inhaler even if you do not taste or feel the medicine.

Step 3. Close

Figure H

- Close the red cap firmly over the mouthpiece. See Figure H.
- Make sure you close the red cap after each inhalation so that the inhaler will be ready for your next dose.
- If you need another dose close the red cap and then repeat steps 1-3.

Storing your PROAIR RESPICLICK inhaler

- Store PROAIR RESPICLICK at room temperature between 59°F and 77°F (15°C and 25°C).
- Avoid exposure to extreme heat, cold, or humidity.
- Keep the red cap on the inhaler closed during storage.
- Keep your PROAIR RESPICLICK inhaler dry and clean at all times.
- Do not wash or put any part of your PROAIR RESPICLICK inhaler in water. Replace your inhaler if washed or placed in water.
- Keep your PROAIR RESPICLICK inhaler and all medicines out of the reach of children.

Cleaning your PROAIR RESPICLICK inhaler

- Do not wash or put any part of your PROAIR RESPICLICK inhaler in water. Replace your inhaler if washed or placed in water.
- PROAIR RESPICLICK contains a powder and must be kept clean and dry at all times.
- If the mouthpiece needs cleaning, gently wipe it with a dry cloth or tissue.

Replacing your PROAIR RESPICLICK inhaler

- The dose counter on the back of your inhaler shows how many doses you have left. Do not try to change the numbers for the dose counter.
- When there are 20 doses left, the dose counter color will change to red, and you should refill your prescription or ask your doctor for another prescription.
- When the dose counter displays ‘0’ your PROAIR RESPICLICK inhaler is empty, and you should stop using the inhaler and throw it away.
- Throw away your PROAIR RESPICLICK inhaler 13 months after removing it from the foil pouch for the first time, when the dose counter displays ‘0’, or after the expiration date on the package, whichever comes first.

Important information

- Do not open the red cap unless you are taking a dose. Repeatedly opening and closing the cap without inhaling a dose will waste the medicine and may damage your inhaler.
- Your PROAIR RESPICLICK inhaler contains dry powder so it is important that you do not blow or breathe into it.
- Do not take the inhaler apart.

Support

- If you have any questions about PROAIR RESPICLICK or how to use your inhaler, go to www.ProAir.com or call 1-888-482-9522.

This Instructions for Use has been approved by the U.S. Food and Drug Administration.

Distributed by:

Teva Pharmaceuticals USA, Inc.

Parsippany, NJ 07054

©2020 Teva Respiratory, LLC. All rights reserved.

PRORIFU-005

Revised September 2020